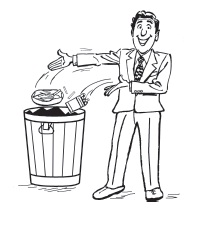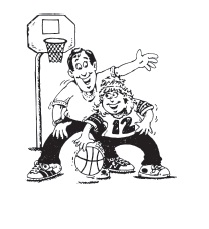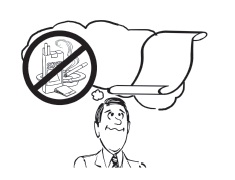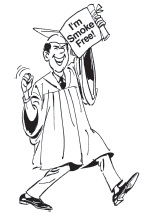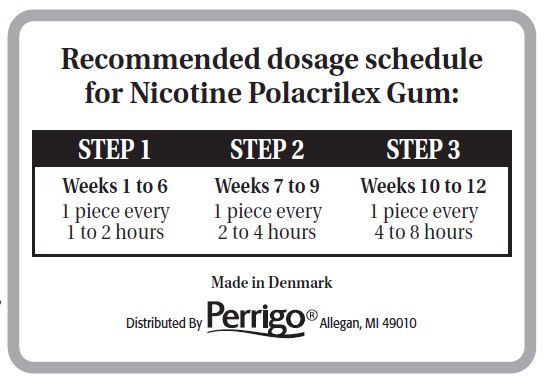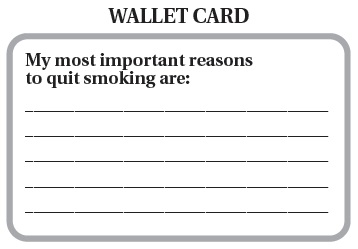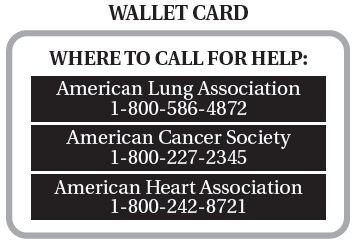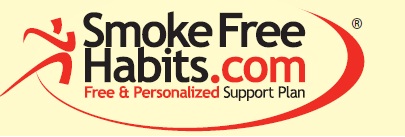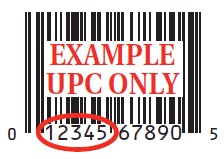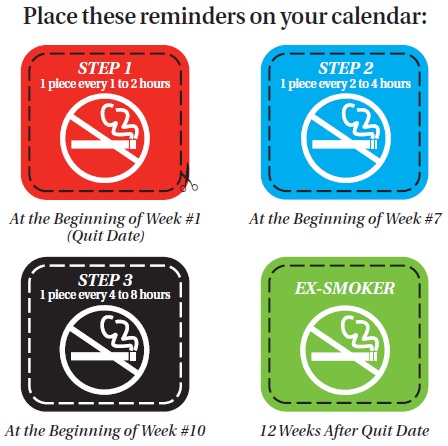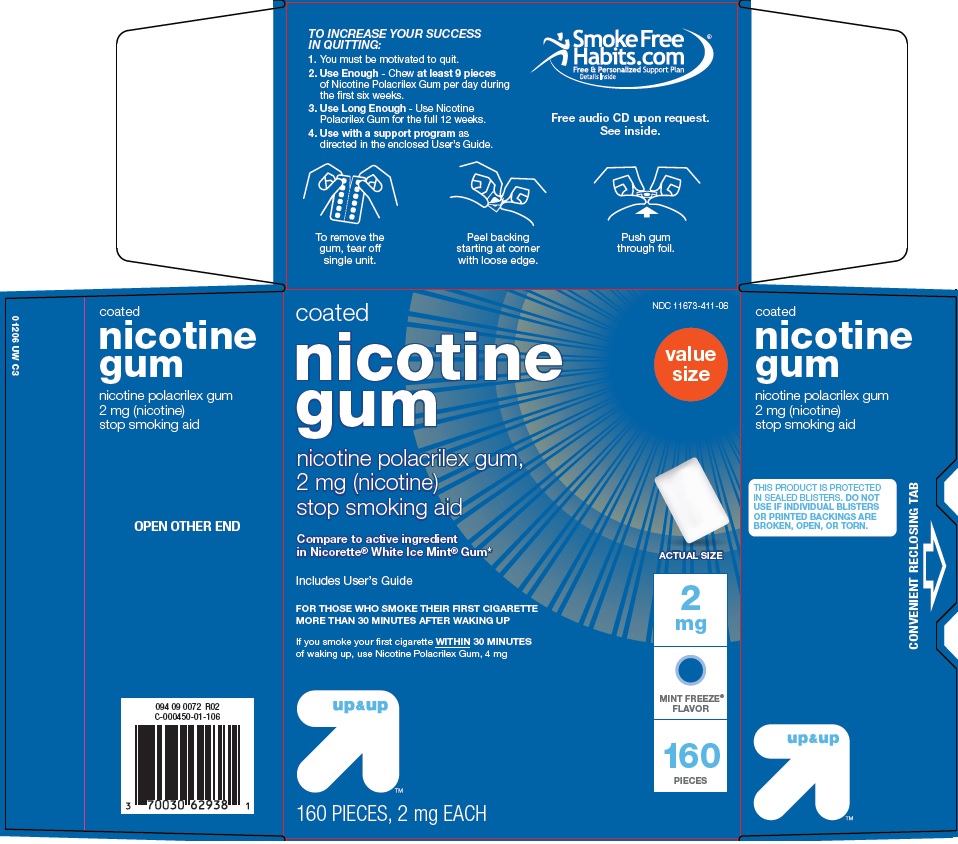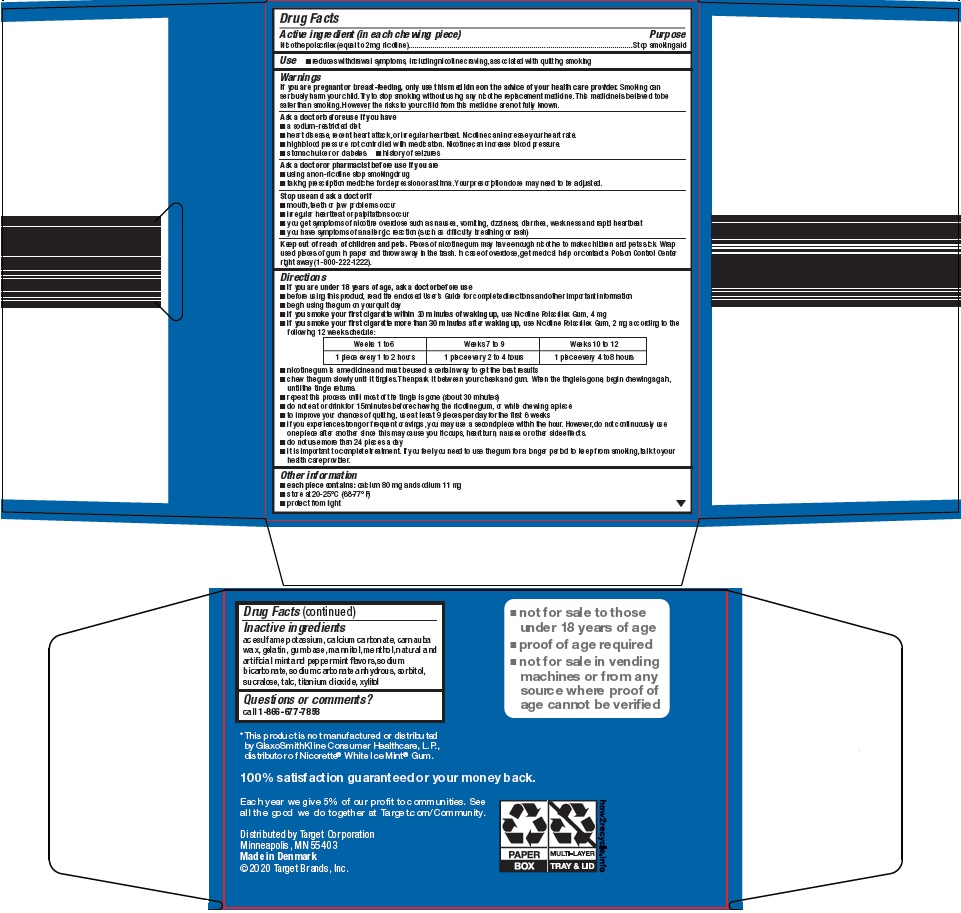 DRUG LABEL: up and up nicotine
NDC: 11673-411 | Form: GUM, CHEWING
Manufacturer: Target Corporation
Category: otc | Type: HUMAN OTC DRUG LABEL
Date: 20260226

ACTIVE INGREDIENTS: NICOTINE 2 mg/1 1
INACTIVE INGREDIENTS: POLACRILIN; ACESULFAME POTASSIUM; CALCIUM CARBONATE; CARNAUBA WAX; GELATIN, UNSPECIFIED; MANNITOL; MENTHOL, UNSPECIFIED FORM; SODIUM BICARBONATE; SODIUM CARBONATE; SORBITOL; SUCRALOSE; TALC; TITANIUM DIOXIDE; XYLITOL

Target Corporation Nicotine Gum Drug Facts

Active ingredient (in each chewing piece)

Nicotine polacrilex (equal to 2 mg nicotine)

Purpose

Stop smoking aid

Use

- reduces withdrawal symptoms, including nicotine craving, associated with quitting smoking

Warnings

If you are pregnant or breast-feeding,

only use this medicine on the advice of your health care provider. Smoking can seriously harm your child. Try to stop smoking without using any nicotine replacement medicine. This medicine is believed to be safer than smoking. However, the risks to your child from this medicine are not fully known.

Ask a doctor before use if you have

- a sodium-restricted diet
- heart disease, recent heart attack, or irregular heartbeat. Nicotine can increase your heart rate.
- high blood pressure not controlled with medication. Nicotine can increase blood pressure.
- stomach ulcer or diabetes
- history of seizures

Ask a doctor or pharmacist before use if you are

- using a non-nicotine stop smoking drug
- taking prescription medicine for depression or asthma. Your prescription dose may need to be adjusted.

Stop use and ask a doctor if

- mouth, teeth or jaw problems occur
- irregular heartbeat or palpitations occur
- you get symptoms of nicotine overdose such as nausea, vomiting, dizziness, diarrhea, weakness and rapid heartbeat
- you have symptoms of an allergic reaction (such as difficulty breathing or rash)

Keep out of reach of children and pets.

Pieces of nicotine gum may have enough nicotine to make children and pets sick. Wrap used pieces of gum in paper and throw away in the trash. In case of overdose, get medical help or contact a Poison Control Center right away (1-800-222-1222).

Directions

- if you are under 18 years of age, ask a doctor before use
- before using this product, read the enclosed User’s Guide for complete directions and other important information
- begin using the gum on your quit day
- if you smoke your first cigarette within 30 minutes of waking up, use Nicotine Polacrilex Gum, 4 mg
- if you smoke your first cigarette more than 30 minutes after waking up, use Nicotine Polacrilex Gum, 2 mg according to the following 12 week schedule:

Weeks 1 to 6 | Weeks 7 to 9 | Weeks 10 to 12
1 piece every; 1 to 2 hours | 1 piece every; 2 to 4 hours | 1 piece every; 4 to 8 hours

- nicotine gum is a medicine and must be used a certain way to get the best results
- chew the gum slowly until it tingles. Then park it between your cheek and gum. When the tingle is gone, begin chewing again, until the tingle returns.
- repeat this process until most of the tingle is gone (about 30 minutes)
- do not eat or drink for 15 minutes before chewing the nicotine gum, or while chewing a piece
- to improve your chances of quitting, use at least 9 pieces per day for the first 6 weeks
- if you experience strong or frequent cravings, you may use a second piece within the hour. However, do not continuously use one piece after another since this may cause you hiccups, heartburn, nausea or other side effects.
- do not use more than 24 pieces a day
- it is important to complete treatment. If you feel you need to use the gum for a longer period to keep from smoking, talk to your health care provider.

Other information

- each piece contains: calcium 80 mg and sodium 11 mg
- store at 20-25oC (68-77oF)
- protect from light

Inactive ingredients

acesulfame potassium, calcium carbonate, carnauba wax, gelatin, gum base, mannitol, menthol, natural and artificial mint and peppermint flavors, sodium bicarbonate, sodium carbonate anhydrous, sorbitol, sucralose, talc, titanium dioxide, xylitol

Questions or comments?

call 1-866-677-7858

Consumer Information

Nicotine Polacrilex Gum

2 mg and 4 mg User’s Guide

How To Use Nicotine Polacrilex Gum To Help You Quit Smoking.

- Not for sale to those under 18 years of age
- Proof of age required
- Not for sale in vending machines or from any source where proof of age cannot be verified

Keys To Success.

1. You must really want to quit smoking for Nicotine Polacrilex Gum to help you.
2. You can greatly increase your chances for success by using a least 9 to 12 pieces every day when you start using Nicotine Polacrilex Gum. See chart on back side of leaflet.
3. You should continue to use Nicotine Polacrilex Gum as explained in this User’s Guide for 12 full weeks. If you feel you need to use Nicotine Polacrilex Gum for a longer period to keep from smoking, talk to your health care provider.
4. Nicotine Polacrilex Gum works best when used together with a support program – See information for instructions on enrollment in the SmokeFreeHabits.com Free & Personalized Support Plan.
5. If you have trouble using Nicotine Polacrilex Gum, ask your doctor, pharmacist or health care professional.
6. To request a free audio CD containing tips to help make quitting easier, call 1-866-677-7858 (ONE CD PER CUSTOMER).

So You Decided To Quit.

Congratulations. Your decision to stop smoking is an important one. That’s why you’ve made the right choice choosing Nicotine Polacrilex Gum. Your own chances of quitting smoking depend on how much you want to quit, how strongly you are addicted to tobacco, and how closely you follow a quitting program like the one that comes with Nicotine Polacrilex Gum.

Quitting Smoking Is Hard!

If you’ve tried to quit before and haven’t succeeded, don’t be discouraged! Quitting isn’t easy. It takes time, and most people try a few times before they are successful. The important thing is to try again until you succeed. This User’s Guide will give you support as you become a nonsmoker. It will answer common questions about Nicotine Polacrilex Gum and give you tips to help you stop smoking, and should be referred to often.

Where To Get Help.

You are more likely to stop smoking by using Nicotine Polacrilex Gum with a support program that helps you break your smoking habit. There may be support groups in your area for people trying to quit. Call your local chapter of the American Lung Association, American Cancer Society or American Heart Association for further information. Toll free phone numbers are printed on the Wallet Card on the bottom of this User’s Guide.

If you find you cannot stop smoking or if you start smoking again after using Nicotine Polacrilex Gum, remember breaking this addiction doesn’t happen overnight. You may want to talk to a health care professional who can help you improve your chances of quitting the next time you try Nicotine Polacrilex Gum or another method.

Let’s Get Organized.

Your reason for quitting may be a combination of concerns about health, the effect of smoking on your appearance, and pressure from your family and friends to stop smoking. Or maybe you’re concerned about the dangerous effects of secondhand smoke on the people you care about. All of these are good reasons. You probably have others. Decide your most important reasons, and write them down on the wallet card on the back of the User’s Guide. Carry this card with you. In difficult moments, when you want to smoke, the card will remind you why you are quitting.

What You’re Up Against.

Smoking is addictive in two ways. Your need for the nicotine has become both physical and mental. You must overcome both addictions to stop smoking. So while Nicotine Polacrilex Gum will lessen your body’s physical addiction to nicotine, you’ve got to want to quit smoking to overcome the mental dependence on cigarettes. Once you’ve decided that you’re going to quit, it’s time to get started. But first, there are some other important warnings you should consider.

Some Important Warnings.

This product is only for those who want to quit smoking. If you are pregnant or breast-feeding, only use this medicine on the advice of your health care provider. Smoking can seriously harm your child. Try to stop smoking without using any nicotine replacement medicine. This medicine is believed to be safer than smoking. However, the risks to your child from this medicine are not fully known.

Ask a doctor before use if you have

- a sodium-restricted diet
- heart disease, recent heart attack, or irregular heartbeat. Nicotine can increase your heart rate.
- high blood pressure not controlled with medication. Nicotine can increase your blood pressure.
- stomach ulcer or diabetes
- history of seizures

Ask a doctor or pharmacist before use if you are

- using a non-nicotine stop smoking drug
- taking a prescription medicine for depression or asthma. Your prescription dose may need to be adjusted.

Stop use and ask a doctor if

- mouth, teeth or jaw problems occur
- irregular heartbeat or palpitations occur
- you get symptoms of nicotine overdose such as nausea, vomiting, dizziness, diarrhea, weakness and rapid heartbeat
- oral blistering occurs (for cinnamon flavor)
- you have symptoms of an allergic reaction (such as difficulty breathing or rash)

Keep out of reach of children and pets. Pieces of nicotine gum may have enough nicotine to make children and pets sick. Wrap used pieces of gum in paper and throw away in trash. In case of overdose, get medical help or contact a Poison Control Center right away (1-800-222-1222).

Let’s Get Started.

Becoming a nonsmoker starts today. First, check that you have bought the right starting dose. If you smoke you first cigarette within 30 minutes of waking up, use Nicotine Polacrilex Gum 4 mg. If you smoke your first cigarette more than 30 minutes after waking up, use Nicotine Polacrilex Gum, 2 mg. Next, read through the entire User’s Guide carefully. Then, set your personalized quitting schedule. Take out a calendar that you can use to track your progress, and identify four dates, using the reminders on the back side of this leaflet:

Step 1. (Weeks 1-6). Your quit date (and the day you’ll start using Nicotine Polacrilex Gum).

Choose your quit date (it should be soon). This is the day you will begin using Nicotine Polacrilex Gum to satisfy your cravings for nicotine. For the first six weeks, you’ll use a piece of Nicotine Polacrilex Gum every hour or two. Be sure to read the How To Use Nicotine Polacrilex Gum section. Place the Step 1 reminder on this date.

Step 2. (Weeks 7-9). The day you’ll start reducing your use of Nicotine Polacrilex Gum

After six weeks, you’ll begin gradually reducing your Nicotine Polacrilex Gum usage to one piece every two to four hours. Place the Step 2 reminder on this date (the first day of week seven).

Step 3. (Weeks 10-12). The day you’ll further reduce you use of Nicotine Polacrilex Gum.

Nine weeks after you begin using Nicotine Polacrilex Gum, you will further reduce your nicotine intake by using one piece every four to eight hours. Place the step 3 reminder on this date (the first day of week ten). For the next three weeks, you’ll use a piece of Nicotine Polacrilex Gum every four to eight hours.

End of treatment: The day you’ll complete Nicotine Polacrilex Gum therapy.

Identify the date thirteen weeks after the date you choose in Step 1, and place the “EX-SMOKER” reminder on your calendar.

Plan Ahead.

Because smoking is an addiction, it is not easy to stop. After you’ve given up cigarettes, you will still have a strong urge to smoke. Plan ahead NOW for these times, so you’re not defeated in a moment of weakness. The following tips may help:

- Keep the phone numbers of supportive friends and family members handy.
- Keep a record of your quitting process. Track the number of Nicotine Polacrilex Gum pieces you use each day, and whether you feel a craving for cigarettes. In the event that you slip, immediately stop smoking and resume your quit attempt with the Nicotine Polacrilex Gum program.
- Put together an Emergency Kit that includes items that will help take your mind off occasional urges to smoke. Include cinnamon gum or lemon drops to suck on, a relaxing CD, and something for your hands to play with, like a smooth rock, rubber band, or small metal balls.
- Set aside some small rewards, like a new magazine or a gift certificate from your favorite store, which you’ll “give” yourself after passing difficult hurdles.
- Think now about the times when you most often want a cigarette, and then plan what else you might do instead of smoking. For instance, you might plan to take your coffee break in a new location, or take a walk right after dinner, so you won’t be tempted to smoke.

How Nicotine Polacrilex Gum Works.

Nicotine Polacrilex Gum sugar-free chewing gum pieces provide nicotine to your system – they work as a temporary aid to help you quit smoking by reducing nicotine withdrawal symptoms. Nicotine Polacrilex Gum provides a lower level of nicotine to your blood than cigarettes, and allows you to gradually do away with your body’s need for nicotine. Because Nicotine Polacrilex Gum does not contain the tar or carbon monoxide of cigarette smoke, it does not have the same health dangers as tobacco. However, it still delivers nicotine, the addictive part of cigarette smoke. Nicotine can cause side effects such as a headache, nausea, upset stomach, and dizziness.

How To Use Nicotine Polacrilex Gum.

If you are under 18 years of age, ask a doctor before use. Before you can use Nicotine Polacrilex Gum correctly, you have to practice! That sounds silly, but isn’t. Nicotine Polacrilex Gum isn’t like ordinary chewing gum. It’s a medicine, and must be chewed a certain way to work right. Chewed like ordinary gum, Nicotine Polacrilex Gum won’t work well and can cause side effects. An overdose can occur if you chew more than one piece of Nicotine Polacrilex Gum at the same time, or if you chew many pieces one after another. Read all the following instructions before using Nicotine Polacrilex Gum. Refer to them often to make sure you’re using Nicotine Polacrilex Gum correctly. If you chew too fast, or do not chew correctly, you may get hiccups, heartburn, or other stomach problems. Don’t eat or drink for 15 minutes before using Nicotine Polacrilex Gum, or while chewing a piece. The effectiveness of Nicotine Polacrilex Gum may be reduced by some foods and drinks, such as coffee, juices, wine or soft drinks.

1. Begin using Nicotine Polacrilex Gum on your quit day.
2. To reduce craving and other withdrawal symptoms, use Nicotine Polacrilex Gum according to the dosage schedule on the back of this leaflet.
3. Chew each Nicotine Polacrilex Gum piece very slowly several times.
4. Stop chewing when you notice a peppery taste, or slight tingling in your mouth. (This usually happens after about 15 chews, but may vary from person to person.)
5. “PARK” the Nicotine Polacrilex Gum piece between your cheek and gum, and leave it there.
6. When the peppery taste and tingle is almost gone (in about minute), start to chew a few times slowly again. When the taste or tingle returns, stop again.
7. Park the Nicotine Polacrilex Gum piece again (in a different place in your mouth).
8. Repeat steps 3 to 7 (chew, chew, park) until most of the nicotine is gone from the Nicotine Polacrilex Gum piece (usually happens in about half an hour; the peppery taste and tingle won’t return.)
9. Wrap the used Nicotine Polacrilex Gum piece in paper and throw in the trash.

The following chart lists the recommended usage schedule for Nicotine Polacrilex Gum:

Weeks 1 to 6

Weeks 7 to 9

Weeks 10 to 12

1 piece every 1 to 2 hours

1 piece every 2 to 4 hours

1 piece every 4 to 8 hours

DO NOT USE MORE THAN 24 PIECES PER DAY.

To improve your chances of quitting, use at least 9 pieces of Nicotine Polacrilex Gum a day. If you experience strong or frequent cravings you may use a second piece within the hour. However, do not continuously use one piece after another, since this may cause you hiccups, heartburn, nausea or other side effects.

How To Reduce Your Nicotine Polacrilex Gum Usage.

The goal of using Nicotine Polacrilex Gum is to slowly reduce your dependence on nicotine. The schedule for using Nicotine Polacrilex Gum will help you reduce your craving gradually as you reduce and then stop your use of Nicotine Polacrilex Gum. Here are some tips to help you cut back during each step and then stop using Nicotine Polacrilex Gum:

- After a while, start chewing each Nicotine Polacrilex Gum piece for only 10 to 15 minutes, instead of half an hour. Then, gradually begin to reduce the number of pieces used.
- Or, try chewing each piece for longer than half an hour, but reduce the number of pieces you use each day.
- Substitute ordinary chewing gum for some of the Nicotine Polacrilex Gum pieces you would normally use. Increase the number of ordinary gum as you cut back on the Nicotine Polacrilex Gum pieces.
- Check how well you’ve reduced your daily usage of Nicotine Polacrilex Gum in Weeks 10 to 12. You should only be using 3 to 5 pieces a day. Get ready to stop.

The following tips may help you try to stop Nicotine Polacrilex Gum when you have completed treatment.

- Set a stop date.
- Use the same number of pieces of confectionary gum or mints as you were using Nicotine Polacrilex Gum per day. At the times when you have an urge to use Nicotine Polacrilex Gum, use a strong flavored gum or mint such as cinnamon or peppermint.
- Reduce the number of pieces of gum or mints you use by one piece per day until you do not need to use any gum or mints.

Talk to your doctor or health care provider if you:

- still feel the need to use Nicotine Polacrilex Gum at the end of week 12 to keep from smoking
- start using Nicotine Polacrilex Gum again after stopping
- start smoking again

Tips To Make Quitting Easier.

Within the first few weeks of giving up smoking, you may be tempted to smoke for pleasure, particularly after completing a difficult task, or at a party or bar. Here are some tips to help get you through the important first stages of becoming a nonsmoker:

On your Quit Date:

- Ask your family, friends and coworkers to support you in your efforts to stop smoking.
- Throw away all your cigarettes, matches, lighters, ashtrays, etc.
- Keep busy on your quit day. Exercise. Go to a movie. Take a walk. Get together with friends.
- Figure out how much money you’ll save by not smoking. Most ex-smokers can save more than $1,000 a year.
- Write down what you will do with the money you save.
- Know your high risk situations and plan ahead how you will deal with them.
- Keep Nicotine Polacrilex Gum near your bed, so you’ll be prepared for any nicotine cravings when you wake up in the morning.
- Visit your dentist and have your teeth cleaned to get rid of the tobacco stains.

Right After Quitting:

- During the first few days after you’ve stopped smoking, spend as much time as possible at places where smoking is not allowed.
- Drink large quantities of water and fruit juices.
- Try to avoid alcohol, coffee and other beverages you associate with smoking.
- Remember that temporary urges to smoke will pass, even if you don’t smoke a cigarette.
- Keep your hands busy with something like a pencil or paper clip.
- Find other activities which help you relax without cigarettes.
- Swim, jog, take a walk, play basketball.
- Don’t worry too much about gaining weight, Watch what you eat, take time for daily exercise, and change your eating habits if you need to.
- Laughter helps. Watch or read something funny.

What to Expect.

Your body is now coming back into balance. During the first few days after you stop smoking, you might feel edgy and nervous and have trouble concentrating. You might get headaches, feel dizzy and a little out of sorts, feel sweaty or have stomach upsets. You might even have trouble sleeping at first. These are typical withdrawal symptoms that will go away with time. Your smoker’s cough will get worse before it gets better. But don’t worry, that’s a good sign. Coughing helps clear the tar deposits out of your lungs.

After A Week Or Two.

By now you should be feeling more confident that you can handle those smoking urges. Many of your withdrawal symptoms have left by now, and you should be noticing some positives signs: less coughing, better breathing and an improved sense of taste and smell, to name a few.

After A Month.

You probably have the urge to smoke less often now. But urges may still occur, and when they do, they are likely to be powerful ones that come out of nowhere. Don’t let them catch you off guard. Plan ahead for these difficult times.

Concentrate on the ways nonsmokers are more attractive than smokers. Their skin is less likely to wrinkle. Their teeth are whiter, cleaner. Their breath is fresher. Their hair and clothes smell better. That cough that seems to make even a laugh sound more like a rattle is a thing of the past. Their children and others around them are healthier, too.

What To Do About Relapse.

What should you do if you slip and start smoking again? The answer is simple. A lapse of one or two or even a few cigarettes has not spoiled your efforts! Discard your cigarettes, forgive yourself and try again. If you start smoking again, keep your box of Nicotine Polacrilex Gum for your next quit attempt.

If you have taken up regular smoking again, don’t be discouraged. Research shows that the best thing you can do is to try again. The important thing is to learn from your last attempt.

- Admit that you’ve slipped, but don’t treat yourself as a failure.
- Try to identify the “trigger” that caused you to slip, and prepare a better plan for dealing with this problem next time.
- Talk positively to yourself – tell yourself that you have learned something from this experience.
- Make sure you used Nicotine Polacrilex Gum correctly over the full 12 weeks to reduce your craving for nicotine.
- Remember that it takes practice to do anything, and quitting smoking is no exception.

When The Struggle Is Over.

Once you’ve stopped smoking, take a second and pat yourself on your back. Now do it again. You deserve it. Remember now why you decided to stop smoking in the first place. Look at your list of reasons. Read them again. And smile. Now think about all the money you are saving and what you’ll do with it. All the nonsmoking places you can go, and what you might do there. All those years you may have added to your life, and what you’ll do with them. Remember that temptation may not be gone forever. However, the hard part is behind you so look forward with a positive attitude, and enjoy your new life as a nonsmoker.

Questions & Answers.

1. How will I feel when I stop smoking and start using Nicotine Polacrilex Gum?

You’ll need to prepare yourself for some nicotine withdrawal symptoms. These begin almost immediately after you stop smoking, are usually at their worst during the first three or four days. Understand that any of the following is possible:

- craving for cigarettes
- anxiety, irritability, restlessness, mood changes, nervousness
- drowsiness
- trouble concentrating
- increased appetite and weight gain
- headaches, muscular pain, constipation, fatigue

Nicotine Polacrilex Gum can help provide relief from withdrawal symptoms such as irritability and nervousness, as well as the craving for nicotine you used to satisfy by having a cigarette.

2. Is Nicotine Polacrilex Gum just substituting one form of nicotine for another?

Nicotine Polacrilex Gum does not contain nicotine. The purpose of Nicotine Polacrilex Gum is to provide you with enough nicotine to help control the physical withdrawal symptoms so you can deal with the mental aspects of quitting. During the 12 week program, you will gradually reduce your nicotine intake by switching to fewer pieces each day.

3. Can I be hurt by using Nicotine Polacrilex Gum?

For most adults, the amount of nicotine in the gum is less than from smoking. Some people will be sensitive to even this amount of nicotine and should not use this product without the advice from their doctor. Check the Some Important Warnings section on the front of this leaflet.

Because Nicotine Polacrilex Gum is a gum-based product, chewing it can cause dental fillings to loosen and aggravate other mouth, tooth, and jaw problems. Nicotine Polacrilex Gum can also cause hiccups, heartburn and other stomach problems especially if chewed too quickly or not chewed correctly.

4. Will I gain weight?

Many people do tend to gain a few pounds the first 8 – 10 weeks after they stop smoking. This is a very small price to pay for the enormous gains that you will make in your overall health and attractiveness. If you continue to gain weight after the first two months, try to analyze what you’re doing differently. Reduce your fat intake, choose healthy snacks, and increase your physical activity to burn off the extra calories.

5. Is Nicotine Polacrilex Gum more expensive than smoking?

The total cost of Nicotine Polacrilex Gum for the twelve week program is about equal to what a person who smokes one and a half packs of cigarettes a day would spend on cigarettes for the same period of time.

Also, use of Nicotine Polacrilex Gum is only short-term cost, while the cost of smoking is a long-term cost, because of the health problems smoking causes.

6. What if I slip up?

Discard your cigarettes, forgive yourself and then get back on track. Don’t consider yourself a failure or punish yourself. In fact, people who have already tried to quit are more likely to be successful the next time.

Good Luck!

: 02952 00 J3

Free Personalized Plan

Begin Right Now!

Having a plan will help you in your efforts to stop smoking. We can help! Follow the simple steps below to receive your valuable personalized Smoke Free Habits plan and many other stop smoking tools and resources.

How To Enroll

Stopping smoking involves breaking your physical addiction and changing your behavior. You will use Nicotine Polacrilex Gum to help break your physical addiction, while your free personalized plan will help you develop healthier behaviors.

To enroll:

- Go online to www.SmokeFreeHabits.com
- Enter the first 5 digits of the UPC number from the box.
- Answer the questions about yourself.
- Print your personalized plan.
  (If you don’t have access to the internet, you can call 1-866-677-7858, answer questions, and your plan will be mailed to you in a few days.)

What You Will Receive

Here are the free tools and resources that you will receive based on how you sign up for the program:

 | Online | By Phone
Personalized 12-Week Plan | immediately | by mail
Buddy Brochure | immediately | by mail
Personal Wellness Assessment | immediately
Week 2 Helpful Tips | X
Week 3 Helpful Tips | X | by mail
Week 4 Helpful Tips | X
Week 6 Helpful Tips | X | by mail
Week 9 Helpful Tips | X
Week 12 Certificate of Accomplishment | X | by mail
Online Drug Database | X
Daily Health News | X

Tips To Get Started

1. Follow your personalized Smoke Free Habits support plan.
2. Be sure to use Nicotine Polacrilex Gum as directed.
3. Throw away all of your cigarettes, lighters, and ashtrays.
4. You may feel urges to smoke, but they usually pass in 2-3 minutes. When you feel an urge, do something else. Take deep breaths and let them out slowly. Drink a glass of water.
5. Carry things to put in your mouth, like gum, hard candy, or toothpicks.
6. Be active, Take a walk with a friend, ride a bike, walk the dog, play tennis.
7. Go to places where you are not allowed to smoke, like the movies or the mall. Try to steer clear of places where you usually smoke, like a break room at work or a favorite bar.
8. Ask friends or family for support whenever you need it.

Package/Label Principal Display Panel

coated

nicotine gum

value size

nicotine polacrilex gum, 2 mg (nicotine)

stop smoking aid

Compare to active ingredient in Nicorette® White Ice Mint® Gum

ACTUAL SIZE

Includes User’s Guide

FOR THOSE WHO SMOKE THEIR FIRST CIGARETTE MORE THAN 30 MINUTES AFTER WAKING UP

If you smoke your first cigarette WITHIN 30 MINUTES of waking up, use Nicotine Polacrilex Gum, 4 mg

2 mg

MINT FREEZE FLAVOR®

160 PIECES

160 PIECES, 2 mg EACH